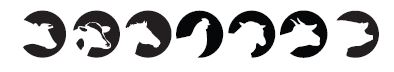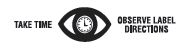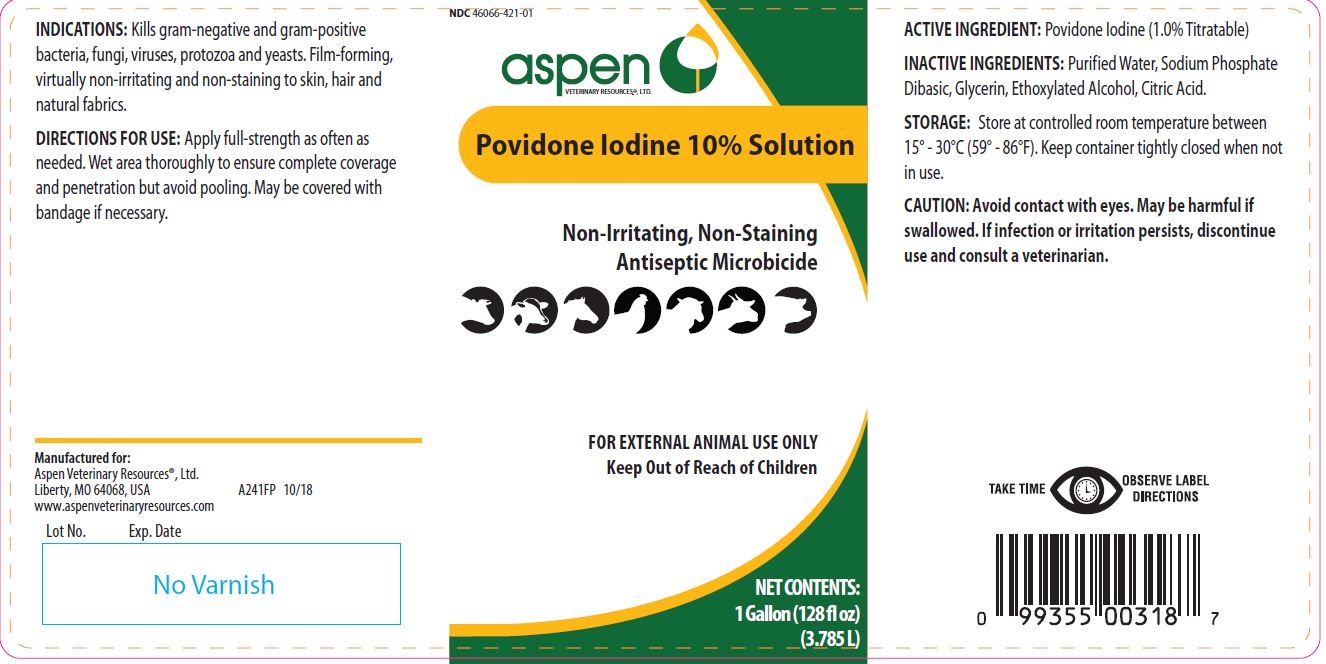 DRUG LABEL: POVIDONE IODINE
NDC: 46066-421 | Form: SOLUTION
Manufacturer: Aspen Veterinary
Category: animal | Type: OTC ANIMAL DRUG LABEL
Date: 20190108

ACTIVE INGREDIENTS: POVIDONE-IODINE 65.9 g/1 L

Povidone Iodine 10% Solution

VETERINARY INDICATIONS

Non-Irritating, Non-Staining Antiseptic Microbicide

KEEP OUT OF REACH OF CHILDREN

FOR EXTERNAL ANIMAL USE ONLY
Keep Out of Reach of Children

INDICATIONS:

Kills gram-negative and gram-positive bacteria, fungi, viruses, protozoa, and yeasts. Film-forming, virtually non-irritating and non-staining to skin, hair, and natural fabrics.

DIRECTIONS FOR USE:

Apply full-strength as often as needed. Wet area thoroughly to ensure complete coverage and penetration but avoid pooling. May be covered with bandage if necessary.

ACTIVE INGREDIENT:

Povidone Iodine (1.0% Titratable)

INACTIVE INGREDIENTS:

Purified Water, Sodium Phosphate Dibasic, Glycerin, Ethoxylated Alcohol, Citric Acid.

STORAGE:

Store at controlled room temperature between 15º-30ºC (59º-86ºF). Keep container tightly closed when not in use.

CAUTION:

Avoid contact with eyes. May be harmful if swallowed. If infection or irritation persists, discontinue use and consult a veterinarian.

NET CONTENTS:

1 Gallon (128 fl oz) (3.785 L)

INFORMATION FOR OWNERS/CAREGIVERS

Manufactured for:
Aspen Veterinary Resources®, Ltd.
Liberty, MO 64068, USA A241FP 10/18
www.aspenveterinaryresources.com